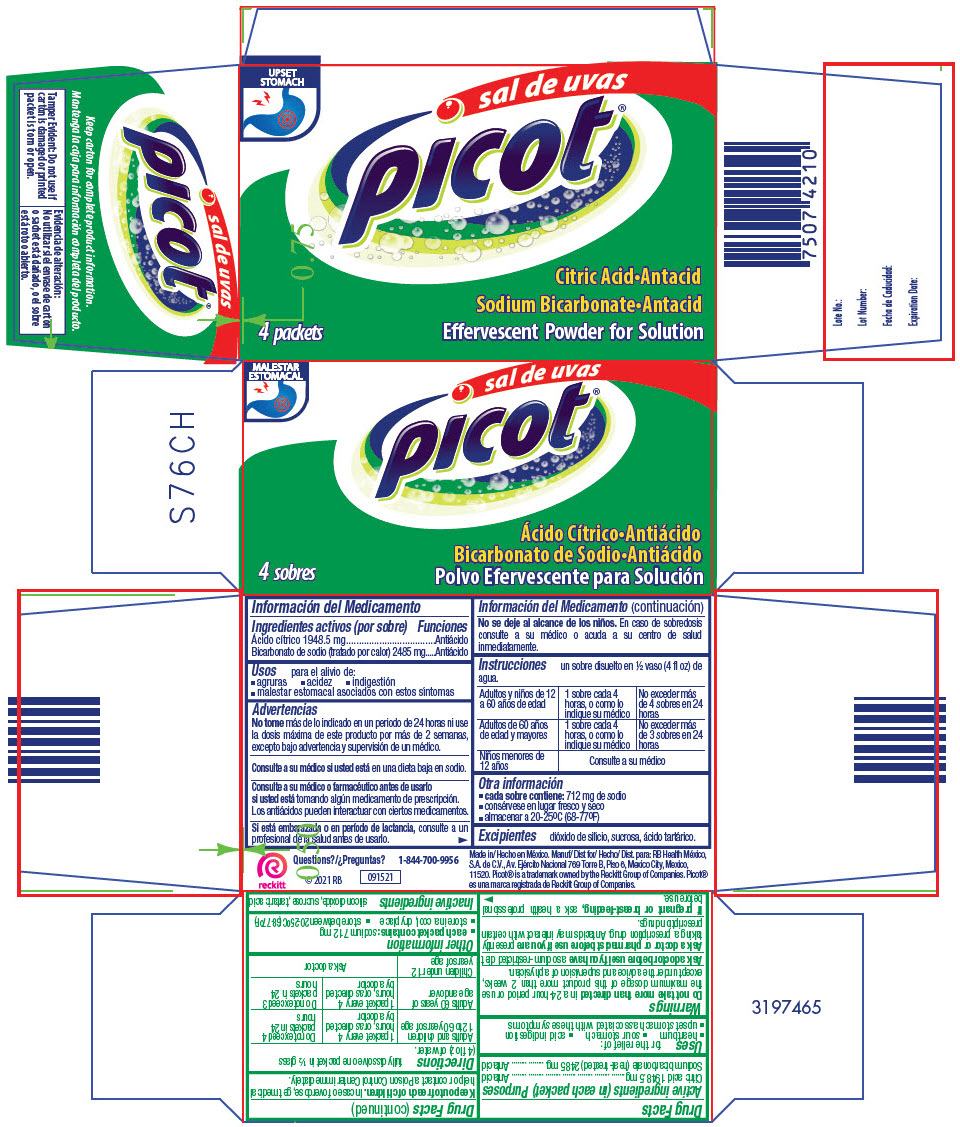 DRUG LABEL: Sal de Uvas Picot
NDC: 73208-580 | Form: GRANULE, EFFERVESCENT
Manufacturer: RB Health Mexico, S.A. de C.V.
Category: otc | Type: HUMAN OTC DRUG LABEL
Date: 20241115

ACTIVE INGREDIENTS: Citric Acid monohydrate 1948.5 mg/1 1; Sodium bicarbonate 2485 mg/1 1
INACTIVE INGREDIENTS: Silicon dioxide; SUCROSE; Tartaric acid

Sal de Uvas Picot®

Drug Facts

ACTIVE INGREDIENT

PURPOSE

Active ingredients (in each packet) | Purposes
Citric acid 1948.5 mg | Antacid
Sodium bicarbonate (heat-treated) 2485 mg | Antacid

Uses

for the relief of:

- heartburn
- sour stomach
- acid indigestion
- upset stomach associated with these symptoms

Warnings

Do not take more than directed in a 24-hour period or use the maximum dosage of this product more than 2 weeks, except under the advice and supervision of a physician.

Ask a doctor before use if you have a sodium-restricted diet

Ask a doctor or pharmacist before use if you are presently taking a prescription drug. Antacids may interact with certain prescription drugs.

PREGNANCY OR BREAST FEEDING

If pregnant or breast-feeding, ask a health professional before use.

Keep out of reach of children. In case of overdose, get medical help or contact a Poison Control Center immediately.

Directions

fully dissolve one packet in ½ glass (4 fl oz) of water.

Adults and children 12 to 60 years of age | 1 packet every 4 hours, or as directed by a doctor | Do not exceed 4 packets in 24 hours
Adults 60 years of age and over | 1 packet every 4 hours, or as directed by a doctor | Do not exceed 3 packets in 24 hours
Children under 12 years of age | Ask a doctor

Other information

- each packet contains: sodium 712 mg
- store in a cool, dry place
- store between 20-25°C (68-77°F)

Inactive ingredients

silicon dioxide, sucrose, tartaric acid.

Questions?

1-844-700-9956

Made in Mexico.

PRINCIPAL DISPLAY PANEL - 4 Packet Carton

UPSET
STOMACH

sal de uvas
picot®

4 packets

Citric Acid•Antacid

Sodium Bicarbonate•Antacid

Effervescent Powder for Solution